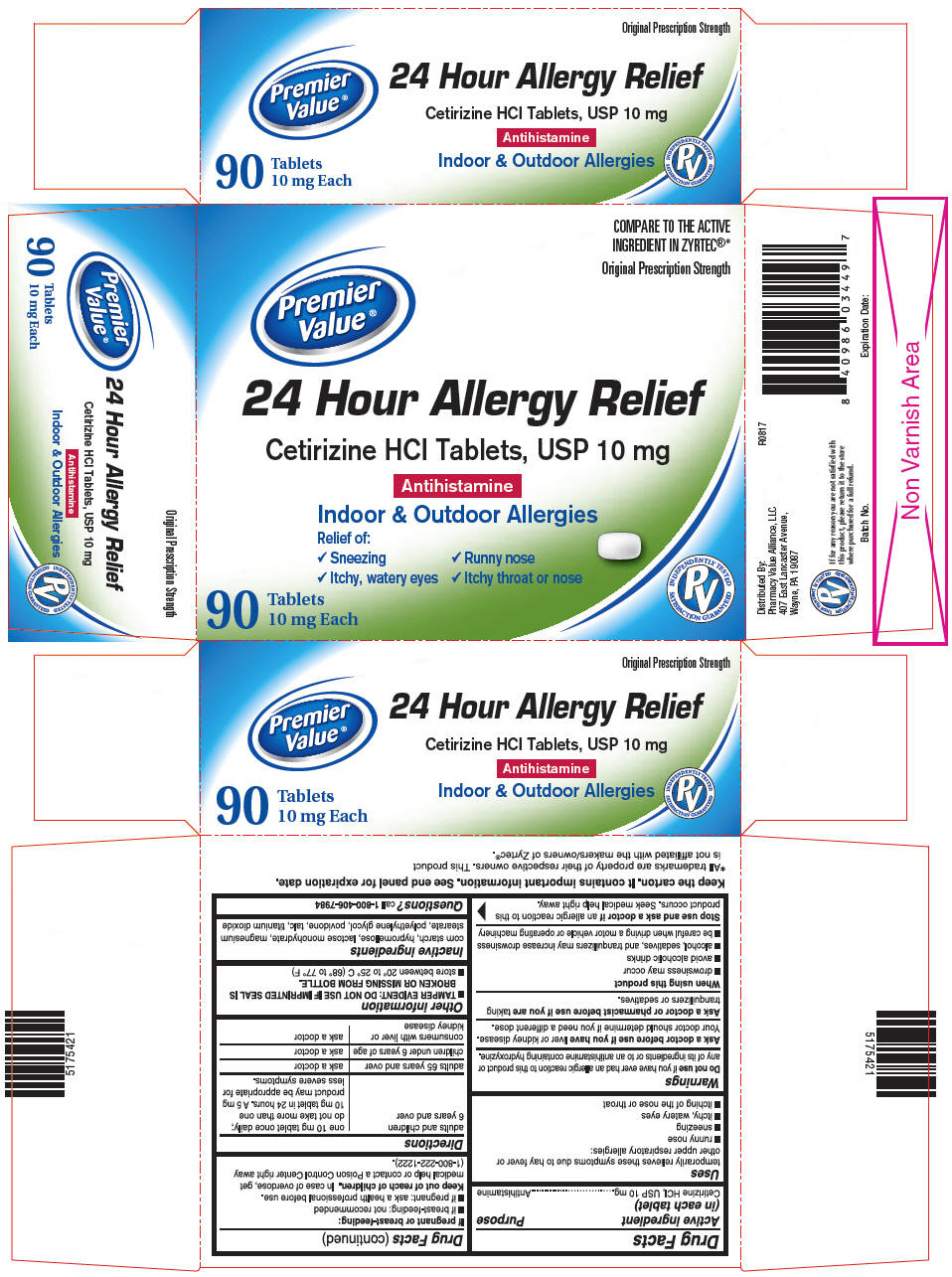 DRUG LABEL: Cetirizine Hydrochloride
NDC: 68016-939 | Form: TABLET
Manufacturer: Chain Drug Consortium, LLC
Category: otc | Type: HUMAN OTC DRUG LABEL
Date: 20180824

ACTIVE INGREDIENTS: CETIRIZINE HYDROCHLORIDE 10 mg/1 1
INACTIVE INGREDIENTS: STARCH, CORN; HYPROMELLOSE, UNSPECIFIED; LACTOSE MONOHYDRATE; MAGNESIUM STEARATE; TALC; TITANIUM DIOXIDE; POLYETHYLENE GLYCOL, UNSPECIFIED; POVIDONE, UNSPECIFIED

Drug Facts

ACTIVE INGREDIENT (IN EACH TABLET)

Cetirizine HCl, USP 10 mg

PURPOSE

Antihistamine

USES

temporarily relieves these symptoms due to hay fever or other upper respiratory allergies:

- runny nose
- sneezing
- itchy, watery eyes
- itching of the nose or throat

WARNINGS

Do not use

if you have ever had an allergic reaction to this product or any of its ingredients or to an antihistamine containing hydroxyzine.

Ask a doctor before use if you have

liver or kidney disease. Your doctor should determine if you need a different dose.

Ask a doctor or pharmacist before use if you are

taking tranquilizers or sedatives.

When using this product

- drowsiness may occur
- avoid alcoholic drinks
- alcohol, sedatives, and tranquilizers may increase drowsiness
- be careful when driving a motor vehicle or operating machinery

Stop use and ask a doctor if

an allergic reaction to this product occurs. Seek medical help right away.

If pregnant or breast-feeding:

- if breast-feeding: not recommended
- if pregnant: ask a health professional before use.

Keep out of reach of children.

In case of overdose, get medical help or contact a Poison Control Center right away (1-800-222-1222).

DIRECTIONS

adults and children 6 years and over | one 10 mg tablet once daily; do not take more than one 10 mg tablet in 24 hours. A 5 mg product may be appropriate for less severe symptoms.
adults 65 years and over | ask a doctor
children under 6 years of age | ask a doctor
consumers with liver or kidney disease | ask a doctor

OTHER INFORMATION

- TAMPER EVIDENT: DO NOT USE IF IMPRINTED SEAL IS BROKEN OR MISSING FROM BOTTLE. (for bottle cartons/stand-alone labels only)
- TAMPER EVIDENT: DO NOT USE IF BLISTER UNITS ARE TORN, BROKEN OR SHOW ANY SIGNS OF TAMPERING. (for blister cartons only)
- store between 20° to 25° C (68° to 77° F)

INACTIVE INGREDIENTS

corn starch, hypromellose, lactose monohydrate, magnesium stearate, polyethylene glycol, povidone, talc, titanium dioxide

QUESTIONS?

call 1-800-406-7984

Keep the carton. It contains important information.

See end panel for expiration date.

Distributed By:
Pharmacy Value Alliance, LLC
407 East Lancaster Avenue,
Wayne, PA 19087

PRINCIPAL DISPLAY PANEL - 10 mg Tablet Bottle Carton

COMPARE TO THE ACTIVE
INGREDIENT IN ZYRTEC®*

Original Prescription Strength

Premier
Value®

24 Hour Allergy Relief

Cetirizine HCl Tablets, USP 10 mg

Antihistamine

Indoor & Outdoor Allergies

Relief of:

✓ Sneezing
✓ Runny nose
✓ Itchy, watery eyes
✓ Itchy throat or nose

90
Tablets
10 mg Each

INDEPENDENTLY TESTED
PV
SATISFACTION GUARANTEED